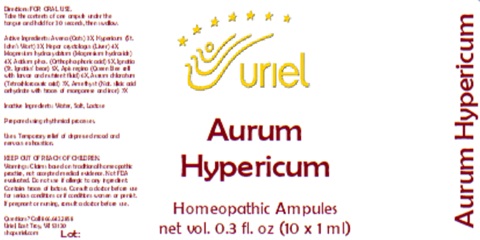 DRUG LABEL: Aurum Hypericum
NDC: 48951-1397 | Form: LIQUID
Manufacturer: Uriel Pharmacy, Inc
Category: homeopathic | Type: HUMAN OTC DRUG LABEL
Date: 20250212

ACTIVE INGREDIENTS: MAGNESIUM HYDROXIDE 4 [hp_X]/1 mL; ROYAL JELLY 6 [hp_X]/1 mL; SILICON DIOXIDE 7 [hp_X]/1 mL; PHOSPHORIC ACID 5 [hp_X]/1 mL; STRYCHNOS IGNATII SEED 5 [hp_X]/1 mL; GOLD TRICHLORIDE 7 [hp_X]/1 mL; ST. JOHN'S WORT 3 [hp_X]/1 mL; AVENA SATIVA FLOWERING TOP 3 [hp_X]/1 mL; ORYCTOLAGUS CUNICULUS LIVER 4 [hp_X]/1 mL
INACTIVE INGREDIENTS: LACTOSE; SODIUM CHLORIDE; WATER

Aurum Hypericum

INDICATIONS AND USAGE

Directions: FOR ORAL USE.

DOSAGE AND ADMINISTRATION

Take the contents of one ampule under the
tongue and hold for 30 seconds, then swallow.

ACTIVE INGREDIENT

Active Ingredients: Avena (Oats) 3X, Hypericum (St. John's Wort) 3X, Hepar oryctolagus (Liver) 4X, Magnesium hydroxydatum (Magnesium hydroxide) 4X, Acidum phos. (Orthophosphoric acid) 5X, Ignatia (St. Ignatius' bean) 5X, Apis regina (Queen Bee cell with larvae and nutrient fluid) 6X, Aurum chloratum (Tetrachloroauric acid) 7X, Amethyst (Nat. silicic acid anhydrate with traces of manganese and iron) 7X

Inactive Ingredients: Water, Salt, Lactose

Prepared using rhythmical processes.

PURPOSE

Uses: Temporary relief of depressed mood and nervous exhaustion.

KEEP OUT OF REACH OF CHILDREN.

WARNINGS

Warnings: Claims based on traditional homeopathic practice, not accepted medical evidence. Not FDA evaluated. Do not use if allergic to any ingredient. Contains traces of lactose. Consult a doctor before use for serious conditions or if conditions worsen or persist. If pregnant or nursing, consult a doctor before use.

Questions? Call 866.642.2858
Uriel, East Troy, WI 53120
shopuriel.com

Lot: